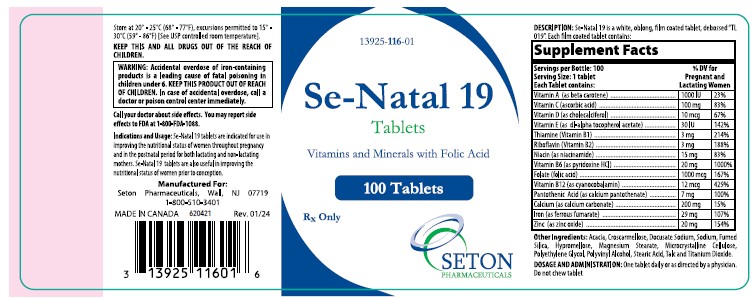 DRUG LABEL: Se-Natal 19
NDC: 13925-116 | Form: TABLET
Manufacturer: Seton Pharmaceuticals
Category: prescription | Type: HUMAN PRESCRIPTION DRUG LABEL
Date: 20250224

ACTIVE INGREDIENTS: .BETA.-CAROTENE 1000 [iU]/1 1; ASCORBIC ACID 100 mg/1 1; CHOLECALCIFEROL 400 [iU]/1 1; .ALPHA.-TOCOPHEROL ACETATE, DL- 30 mg/1 1; THIAMINE 3 mg/1 1; RIBOFLAVIN 3 mg/1 1; NIACINAMIDE 15 mg/1 1; PYRIDOXINE HYDROCHLORIDE 20 mg/1 1; FOLIC ACID 1 mg/1 1; CYANOCOBALAMIN 12 ug/1 1; CALCIUM PANTOTHENATE 7 mg/1 1; CALCIUM CARBONATE 200 mg/1 1; FERROUS FUMARATE 29 mg/1 1; ZINC OXIDE 20 mg/1 1; DOCUSATE SODIUM 25 mg/1 1
INACTIVE INGREDIENTS: ACACIA; CROSCARMELLOSE SODIUM; SILICON DIOXIDE; HYPROMELLOSES; MAGNESIUM STEARATE; CELLULOSE, MICROCRYSTALLINE; POLYETHYLENE GLYCOL, UNSPECIFIED; POLYVINYL ALCOHOL; STEARIC ACID; TALC; TITANIUM DIOXIDE

Se-Natal 19 Tablets

Vitamins & Minerals with Folic Acid

Rx Only

DESCRIPTION

Se-Natal 19 is a white, oblong, film coated tablet, debossed "TL 019". Each film coated tablet contains:

Supplement Facts
Servings per Bottle: 100
Serving Size: 1 tablet
Each Tablet contains: |  | % DV for Pregnant and Lactating Women
Vitamin A (as beta carotene) | 1000 IU | 23%
Vitamin C (ascorbic acid) | 100 mg | 83%
Vitamin D (as cholecalciferol) | 10 mcg | 67%
Vitamin E (as dl-alpha tocoperol acetate) | 30 IU | 142%
Thiamine (Vitamin B1) | 3 mg | 214%
Riboflavin (Vitamin B2) | 3 mg | 188%
Niacin (as niacinamide) | 15 mg | 83%
Vitamin B6 (as pyridoxine HCl) | 20 mg | 1000%
Folate (folic acid) | 1000 mcg | 167%
Vitamin B12 (as cyanocobalamin) | 12 mcg | 429%
Pantothenic Acid (as calcium pantothenate) | 7 mg | 100%
Calcium (as calcium carbonate) | 200 mg | 15%
Iron (as ferrous fumarate) | 29 mg | 107%
Zinc (as zinc oxide) | 20 mg | 154%

OTHER INGREDIENTS

Acacia, Croscarmellose Sodium, Fumed Silica, Hypromellose, Magnesium Stearate, Microcrystalline Cellulose, Polyethylene Glycol, Polyvinyl Alcohol, Stearic Acid, Talc and Titanium Dioxide.

INDICATIONS

Se-Natal 19 tablets are indicated for use in improving the nutritional status of women throughout pregnancy and in the postnatal period for both lactating and non-lactating mothers. Se-Natal 19 tablets are also useful in improving the nutritional status of women prior to conception.

CONTRAINDICATIONS

This product is contraindicated in patients with a known hypersensitivity to any of the ingredients.

WARNINGS

Folic acid alone is improper therapy in the treatment of pernicious anemia and other megaloblastic anemias where vitamin B12 is deficient.

BOXED WARNING

WARNING: Accidental overdose of iron-containing products is a leading cause of fatal poisoning in children under 6. KEEP THIS PRODUCT OUT OF REACH OF CHILDREN. In case of accidental overdose, call a doctor or poison control center immediately.

PRECAUTIONS

General

Take 2 hours after meals. Do not exceed recommended dose. Discontinue use if symptoms of intolerance appear.

Folic Acid

Folic acid in doses above 0.1 mg daily may obscure pernicious anemia, in that hematologic remission can occur while neurological manifestations remain progressive.

Pediatric Use

Safety and effectiveness in pediatric patients have not been established.

Geriatric Use

Dosing for elderly patients should be cautious. Due to the greater frequency of decreased hepatic, renal, or cardiac function, and of concomitant disease or other drug therapy, dosing should start at the lower end of the dosing range.

ADVERSE REACTIONS

Adverse reactions with iron therapy may include GI irritation, constipation, diarrhea, nausea, vomiting, and dark stools. Adverse reactions with iron therapy are usually transient. Allergic sensitization has been reported following both oral and parenteral administration of folic acid.

DRUG INTERACTIONS

Prescriber should be aware of a number of iron/drug interactions, including antacids, tetracyclines, or fluoroquinolones.

OVERDOSAGE

Symptoms:

Abdominal pain, metabolic acidosis, anuria, CNS damage, coma, convulsions, death, dehydration, diffuse vascular congestion, hepatic cirrhosis, hypotension, hypothermia, lethargy, nausea, vomiting, diarrhea, tarry stools, melena, hematemesis, tachycardia, hyperglycemia, drowsiness, pallor, cyanosis, lassitude, seizures, and shock.

DOSAGE AND ADMINISTRATION

One tablet daily, or as directed by a physician.

NOTICE

Contact with moisture can discolor or erode the tablet. Do not chew tablet.

HOW SUPPLIED

Se-Natal 19 tablets for oral administration are supplied as white, coated, oblong tablets debossed "TL019", packaged in bottles of 100 tablets.

Product Code: 13925-116-01.

STORAGE

Store at 20° - 25°C (68° - 77°F), excursions permitted to 15° - 30°C (59° - 86°F) [See USP controlled room temperature].

PHARMACIST

Dispense in a tight, light-resistant container as defined in the USP/NF with child-resistant closure.

Call your doctor about side effects. You may report side effects to FDA at 1-800-FDA-1088.

All prescriptions using this product shall be pursuant to state statutes as applicable. This is not an Orange Book product. This product may be administered only under a physician's supervision. There are no implied or explicit claims on therapeutic equivalence.

Reserved for Professional Recommendation.

KEEP THIS AND ALL DRUGS OUT OF THE REACH OF CHILDREN.

Rx Only

Manufactured For:
Seton Pharmaceuticals
Manasquan, NJ 08736
1-800-510-3401

MADE IN CANADA

Code 116-01

Rev. 03/18

SETON PHARMACEUTICALS

PACKAGE LABEL.PRINCIPAL DISPLAY PANEL

NDC 13925-116-01

Se-Natal 19
Tablets

Vitamins and Minerals with Folic Acid

100 Tablets

Rx Only

SETON
PHARMACEUTICALS